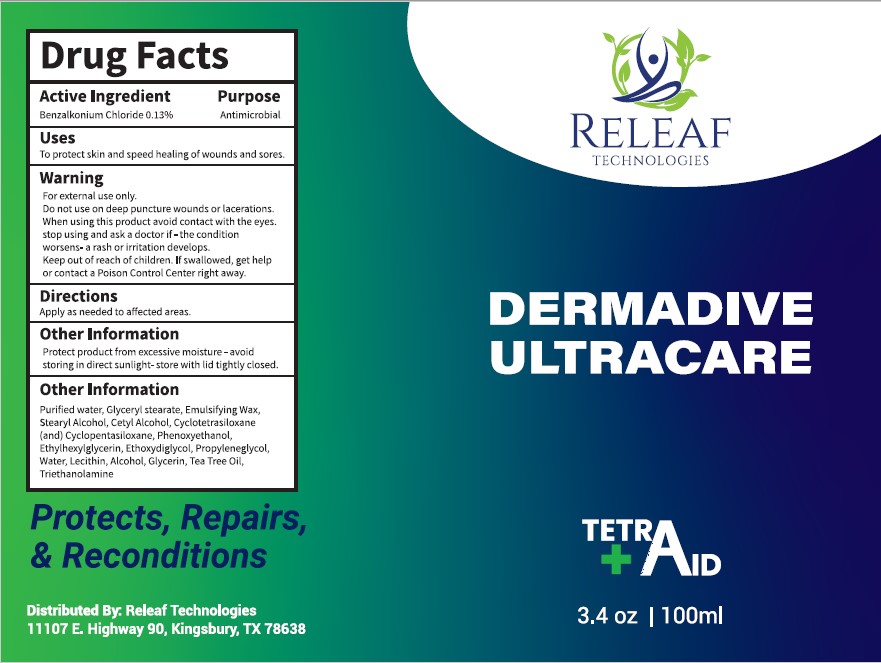 DRUG LABEL: DERMADIVE ULTRACARE - TETRAID
NDC: 78663-102 | Form: LOTION
Manufacturer: Releaf Technologies LLC
Category: otc | Type: HUMAN OTC DRUG LABEL
Date: 20250109

ACTIVE INGREDIENTS: BENZALKONIUM CHLORIDE 0.13 g/100 mL
INACTIVE INGREDIENTS: GLYCERIN; GLYCERYL MONOSTEARATE; WATER; ETHYLHEXYLGLYCERIN; DIETHYLENE GLYCOL MONOETHYL ETHER; POLYSORBATE 60; PHENOXYETHANOL; LECITHIN, SOYBEAN; TROLAMINE; STEARYL ALCOHOL; CYCLOMETHICONE 4; PROPYLENE GLYCOL; CETYL ALCOHOL; TEA TREE OIL; ALCOHOL; CYCLOMETHICONE 5

RELEAF TECHNOLOGIES (as PLD) - DERMADIVE ULTRACARE - TETRAID (78663-102)

ACTIVE INGREDIENT

BENZALKONIUM CHLORIDE 0.13%

PURPOSE

ANTIMICROBIAL

USES

TO PROTECT SKIN AND SPEED HEALING OF WOUNDS AND SORES.

WARNING

FOR EXTERNAL USE ONLY.

DO NOT USE ON DEEP PUNCTURE WOUNDS OR LACERATIONS.

WHEN USING THIS PRODUCT AVOID CONTACT WITH THE EYES.

STOP USING AND ASK A DOCTOR IF

- THE CONDITION WORSENS
- A RASH OR IRRITATION DEVELOPS.

Keep out of reach of children. If swallowed, get medical help or contact a Poison Control Center right away.

DIRECTIONS

APPLY AS NEEDED TO AFFECTED AREAS.

OTHER INFORMATION

PROTECT PRODUCT FROM EXCESSIVE MOISTURE - AVOID STORING IN DIRECT SUNLIGHT - STORE WITH LID TIGHTLY CLOSED.

INACTIVE INGREDIENTS

PURIFIED WATER, GLYCERYL STEARATE, EMULSIFYING WAX, STEARYL ALCOHOL, CETYL ALCOHOL, CYCLOTETRASILOXANE (AND) CYCLOPENTASILOXANE, PHENOXYETHANOL, ETHYLHEXYLGLYCERIN, ETHOXYDIGLYCOL, PROPYLENE GLYCOL, WATER, LECITHIN, ALCOHOL, GLYCERIN, TEA TREE OIL, TRIETHANOLAMINE